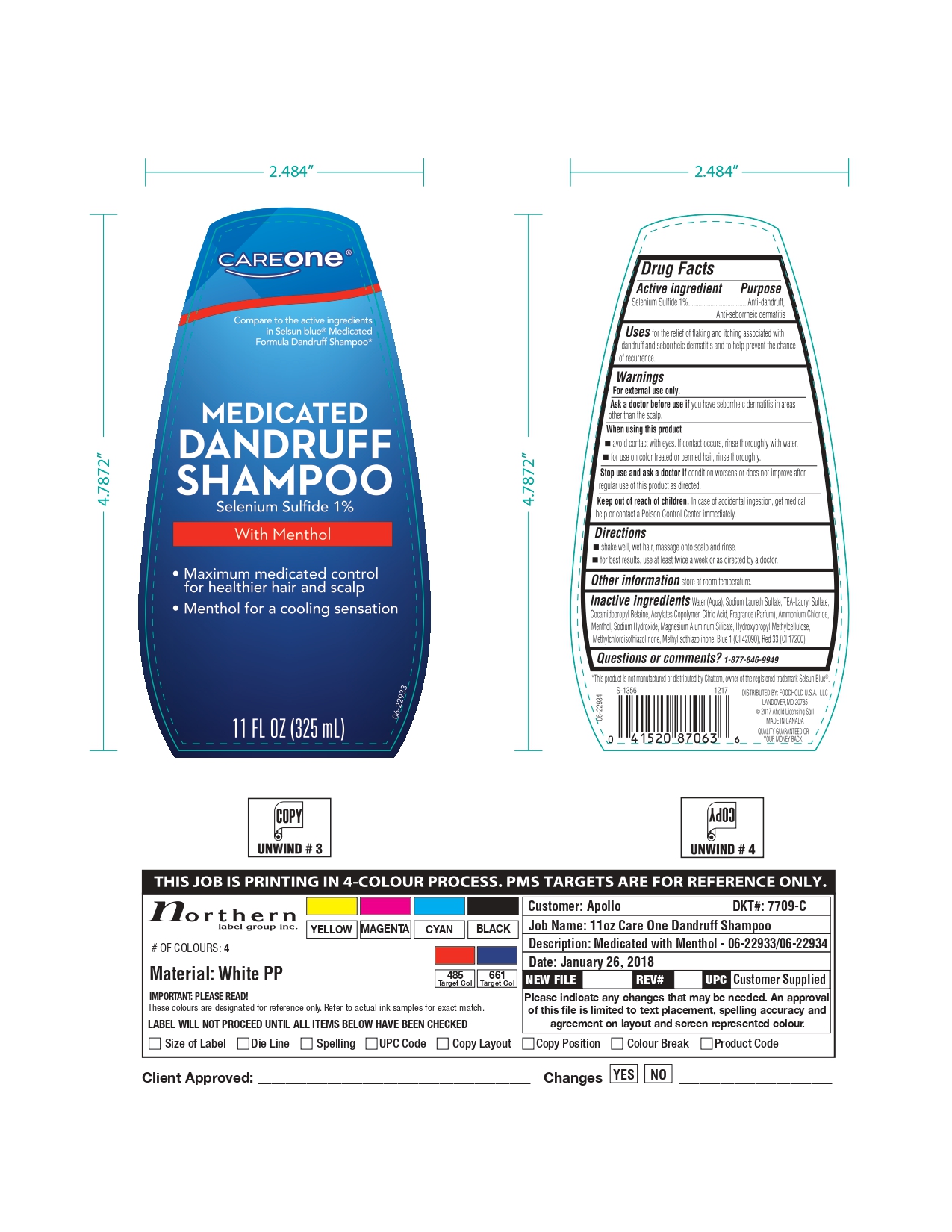 DRUG LABEL: Careone Medicated Dandruff
NDC: 72476-025 | Form: SHAMPOO
Manufacturer: Retail Business Services, LLC
Category: otc | Type: HUMAN OTC DRUG LABEL
Date: 20250206

ACTIVE INGREDIENTS: SELENIUM SULFIDE 10 mg/1 mL
INACTIVE INGREDIENTS: ACRYLATES/VINYL ISODECANOATE CROSSPOLYMER (10000 MPA.S NEUTRALIZED AT 0.5%); SODIUM LAURETH SULFATE; CITRIC ACID MONOHYDRATE; MENTHOL; SODIUM HYDROXIDE; HYPROMELLOSE, UNSPECIFIED; METHYLCHLOROISOTHIAZOLINONE; METHYLISOTHIAZOLINONE; FD&C BLUE NO. 1; D&C RED NO. 33; WATER; TRIETHANOLAMINE LAURYL SULFATE; COCAMIDOPROPYL BETAINE; FRAGRANCE CLEAN ORC0600327; AMMONIUM CHLORIDE; MAGNESIUM ALUMINUM SILICATE

72476-025-03 Careone medicated Dandruff shampoo

Active Ingredient

Selenium Sulfide 1%

Purpose

Anti-dandruff, Anti-seborrheic dermatitis

Uses

for the relief of flaking and itching associated with dandruff and seborrheic dermatitis and to help prevent the chance of recurrence.

Warnings

For external use only.

Ask a doctor before use

you have seborrheic dermatitis in areas other than the scalp.

When using this Product

- Avoid contact with eyes. If contact occurs, rinse thoroughly with water.
- For use on color treated or permed hair, rinse thoroughly.

Stop use and ask a doctor if

Condition worsens or does not improve after regular use of this product as directed.

Keep out of reach of children

In case of accidental ingestion, get medical help or contact a Poison Control Center immediately.

Directions

- Shake well, wet hair, massage onto scalp and rinse.
- For best results, use at least twice a week or as directed by a doctor.

Other Information

Store at Room Temperature

Inactive Ingredients

Water (Aqua), Sodium Laureth Sulfate, TEA-Lauryl Sulfate, Cocamidopropyl Betaine, Acrylates Copolymer, Citric Acid, Fragrance (Parfum), Ammonium Chloride, Menthol, Sodium Hydroxide, Magnesium Aluminium Silicate, Hydroxypropyl Methylcellulose, Methylchloroisothiazolinone, Methylisothiazolinone, Blue 1 (Cl 42090), Red 33 (Cl 17200).

Questions or comments ?

1-877-846-9949